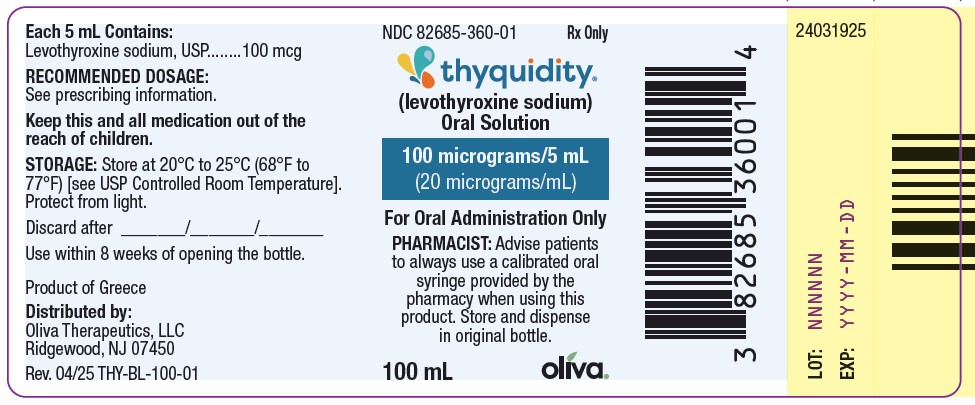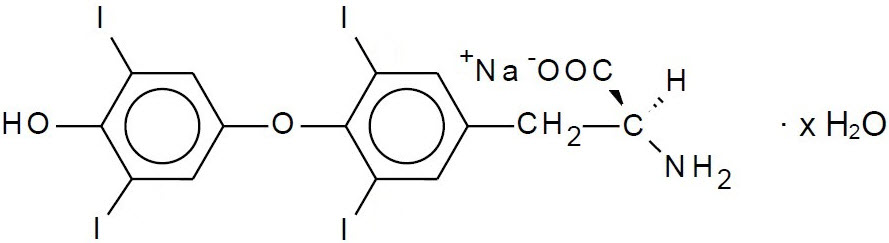 DRUG LABEL: THYQUIDITY
NDC: 82685-360 | Form: SOLUTION
Manufacturer: Oliva Therapeutics, LLC
Category: prescription | Type: HUMAN PRESCRIPTION DRUG LABEL
Date: 20250703

ACTIVE INGREDIENTS: LEVOTHYROXINE SODIUM 100 ug/5 mL
INACTIVE INGREDIENTS: GLYCERIN; CITRIC ACID MONOHYDRATE; METHYLPARABEN SODIUM; SODIUM HYDROXIDE; WATER

HIGHLIGHTS OF PRESCRIBING INFORMATION

These highlights do not include all the information needed to use THYQUIDITY®safely and effectively. See full prescribing information for THYQUIDITY®.
THYQUIDITY®(levothyroxine sodium) oral solution
Initial U.S. Approval: 2000

WARNING: NOT FOR TREATMENT OF OBESITY OR FOR WEIGHT LOSS

See full prescribing information for complete boxed warning

- Thyroid hormones, including THYQUIDITY, should not be used for the treatment of obesity or for weight loss.
- Doses beyond the range of daily hormonal requirements may produce serious or even life-threatening manifestations of toxicity (6, 10).

1 INDICATIONS AND USAGE

THYQUIDITY is levothyroxine sodium (T4) indicated for:

- Hypothyroidism: As replacement therapy in primary (thyroidal), secondary (pituitary), and tertiary (hypothalamic) congenital or acquired hypothyroidism. (1)
- Pituitary Thyrotropin (Thyroid-Stimulating Hormone, TSH) Suppression: As an adjunct to surgery and radioiodine therapy in the management of thyrotropin-dependent well-differentiated thyroid cancer. (1)
  Limitations of Use:
  - Not indicated for suppression of benign thyroid nodules and nontoxic diffuse goiter in iodine-sufficient patients
  - Not indicated for treatment of hypothyroidism during the recovery phase of subacute thyroiditis

2 DOSAGE AND ADMINISTRATION

- Administer once daily, preferably on an empty stomach, one-half to one hour before breakfast. (2.1)
- Administer at least 4 hours before or after drugs that are known to interfere with absorption. (2.1)
- Administer orally using syringe provided by the pharmacy (2.1)
- Evaluate the need for dose adjustments when regularly administering within one hour of certain foods that may affect THYQUIDITY absorption. (2.1)
- Starting dose depends on a variety of factors, including age, body weight, cardiovascular status, and concomitant medical conditions (including pregnancy), concomitant medications, co-administered food, and the specific nature of the condition being treated. Peak therapeutic effect may not be attained for 4-6 weeks. (2.2)
- See full prescribing information for dosing in specific patient populations. (2.3)
- Adequacy of therapy determined with periodic monitoring of TSH and/or T4 as well as clinical status. (2.4)

3 DOSAGE FORMS AND STRENGTHS

Oral Solution: 100 mcg per 5 mL (20 mcg per mL) in 100 mL bottles (3)

4 CONTRAINDICATIONS

- Uncorrected adrenal insufficiency. (4)

5 WARNINGS AND PRECAUTIONS

- Cardiac adverse reactions in the elderly and in patients with underlying cardiovascular disease:Initiate THYQUIDITY at less than the full replacement dose because of the increased risk of cardiac adverse reactions, including atrial fibrillation. (2.3, 5.1, 8.5)
- Myxedema coma:Do not use oral thyroid hormone drug products to treat myxedema coma. (5.2)
- Acute adrenal crisis in patients with concomitant adrenal insufficiency:Treat with replacement glucocorticoids prior to initiation of THYQUIDITY treatment. (5.3)
- Prevention of hyperthyroidism or incomplete treatment of hypothyroidism:Proper dose titration and careful monitoring is critical to prevent the persistence of hypothyroidism or the development of hyperthyroidism. (5.4)
- Worsening of diabetic control:Therapy in patients with diabetes mellitus may worsen glycemic control and result in increased antidiabetic agent or insulin requirements. Carefully monitor glycemic control after starting, changing, or discontinuing thyroid hormone therapy. (5.5)
- Decreased bone mineral density associated with thyroid hormone over- replacement:Over-replacement can increase bone resorption and decrease bone mineral density. Give the lowest effective dose. (5.6)

6 ADVERSE REACTIONS

Adverse reactions associated with THYQUIDITY therapy are primarily those of hyperthyroidism due to therapeutic overdosage: arrhythmias, myocardial infarction, dyspnea, muscle spasm, headache, nervousness, irritability, insomnia, tremors, muscle weakness, increased appetite, weight loss, diarrhea, heat intolerance, menstrual irregularities, and skin rash. (6)

To report SUSPECTED ADVERSE REACTIONS, contact Oliva Therapeutics, LLC at 1-877-200-6088 or FDA at 1-800-FDA-1088 or www.fda.gov/medwatch.

7 DRUG INTERACTIONS

See full prescribing information for drugs that affect thyroid hormone pharmacokinetics (e.g., absorption, synthesis, secretion, metabolism, protein binding, and target tissue response) and may alter the therapeutic response to THYQUIDITY. (7)

8 USE IN SPECIFIC POPULATIONS

Pregnancy may require the use of higher doses of THYQUIDITY. (2.3, 8.1)

FULL PRESCRIBING INFORMATION

WARNING: NOT FOR TREATMENT OF OBESITY OR FOR WEIGHT LOSS

Thyroid hormones, including THYQUIDITY, either alone or with other therapeutic agents, should not be used for the treatment of obesity or for weight loss.

In euthyroid patients, doses within the range of daily hormonal requirements are ineffective for weight reduction.

Larger doses may produce serious or even life threatening manifestations of toxicity, particularly when given in association with sympathomimetic amines such as those used for their anorectic effects [see Adverse Reactions (6), Drug Interactions (7.7), and Overdosage (10)].

1 INDICATIONS AND USAGE

Hypothyroidism

THYQUIDITY is indicated as a replacement therapy in primary (thyroidal), secondary (pituitary), and tertiary (hypothalamic) congenital or acquired hypothyroidism.

Pituitary Thyrotropin (Thyroid-Stimulating Hormone, TSH) Suppression

THYQUIDITY is indicated as an adjunct to surgery and radioiodine therapy in the management of thyrotropin-dependent well-differentiated thyroid cancer.

Limitations of Use:

- THYQUIDITY is not indicated for suppression of benign thyroid nodules and nontoxic diffuse goiter in iodine-sufficient patients as there are no clinical benefits and overtreatment with THYQUIDITY may induce hyperthyroidism [see Warnings and Precautions (5.4)].
- THYQUIDITY is not indicated for treatment of hypothyroidism during the recovery phase of subacute thyroiditis.

2 DOSAGE AND ADMINISTRATION

2.1 General Administration Information

Administer THYQUIDITY as a single daily oral dose, on an empty stomach, one-half to one hour before breakfast.

Administer THYQUIDITY at least 4 hours before or after drugs known to interfere with THYQUIDITY absorption [see Drug Interactions (7.1)].

Evaluate the need for dose adjustments when regularly administering within one hour of certain foods that may affect THYQUIDITY absorption [see Drug Interactions (7.9)and Clinical Pharmacology (12.3)].

Administer THYQUIDITY directly to the mouth using a calibrated oral syringe provided by the pharmacy. A household teaspoon or tablespoon is not an adequate measuring device.

2.2 General Principles of Dosing

The dose of THYQUIDITY for hypothyroidism or pituitary TSH suppression depends on a variety of factors including: the patient's age, body weight, cardiovascular status, concomitant medical conditions (including pregnancy), concomitant medications, co-administered food and the specific nature of the condition being treated [see Dosage and Administration (2.3), Warnings and Precautions (5), and Drug Interactions (7)]. Dosing must be individualized to account for these factors and dose adjustments made based on periodic assessment of the patient's clinical response and laboratory parameters [see Dosage and Administration (2.4)].

The peak therapeutic effect of a given dose of THYQUIDITY may not be attained for 4 to 6 weeks.

2.3 Dosing in Specific Patient Populations

Primary Hypothyroidism in Adults and in Adolescents in Whom Growth and Puberty are Complete

Start THYQUIDITY at the full replacement dose in otherwise healthy, non-elderly individuals who have been hypothyroid for only a short time (such as a few months). The average full replacement dose of THYQUIDITY is approximately 1.6 mcg per kg per day (for example: 100 to 125 mcg per day for a 70 kg adult).

Adjust the dose by 12.5 to 25 mcg increments every 4 to 6 weeks until the patient is clinically euthyroid and the serum TSH returns to normal. Doses greater than 200 mcg per day are seldom required. An inadequate response to daily doses of greater than 300 mcg per day is rare and may indicate poor compliance, malabsorption, drug interactions, or a combination of these factors.

For elderly patients or patients with underlying cardiac disease, start with a dose of 12.5 to 25 mcg per day. Increase the dose every 6 to 8 weeks, as needed, until the patient is clinically euthyroid and the serum TSH returns to normal. The full replacement dose of THYQUIDITY may be less than 1 mcg per kg per day in elderly patients.

In patients with severe longstanding hypothyroidism, start with a dose of 12.5 to 25 mcg per day. Adjust the dose in 12.5 to 25 mcg increments every 2 to 4 weeks until the patient is clinically euthyroid and the serum TSH level is normalized.

Secondary or Tertiary Hypothyroidism

Start THYQUIDITY at the full replacement dose in otherwise healthy, non-elderly individuals. Start with a lower dose in elderly patients, patients with underlying cardiovascular disease or patients with severe longstanding hypothyroidism as described above. Serum TSH is not a reliable measure of THYQUIDITY dose adequacy in patients with secondary or tertiary hypothyroidism and should not be used to monitor therapy. Use the serum free-T4 level to monitor adequacy of therapy in this patient population. Titrate THYQUIDITY dosing per above instructions until the patient is clinically euthyroid and the serum free-T4 level is restored to the upper half of the normal range.

Pediatric Dosage - Congenital or Acquired Hypothyroidism

The recommended daily dose of THYQUIDITY in pediatric patients with hypothyroidism is based on body weight and changes with age as described in Table 1. Start THYQUIDITY at the full daily dose in most pediatric patients. Start at a lower starting dose in newborns (0-3 months) at risk for cardiac failure and in children at risk for hyperactivity (see below). Monitor for clinical and laboratory response [see Dosage and Administration (2.4)].

Table 1. THYQUIDITY Dosing Guidelines for Pediatric Hypothyroidism

AGE | Daily Dose Per Kg Body Weighta
0-3 months | 10-15 mcg/kg/day
3-6 months | 8-10 mcg/kg/day
6-12 months | 6-8 mcg/kg/day
1-5 years | 5-6 mcg/kg/day
6-12 years | 4-5 mcg/kg/day
Greater than 12 years but growth and puberty incomplete | 2-3 mcg/kg/day
Growth and puberty complete | 1.6 mcg/kg/day
aThe dose should be adjusted based on clinical response and laboratory parameters [see Dosage and Administration (2.4)and Use in Specific Populations (8.4)].

Newborns (0-3 months) at risk for cardiac failure: Consider a lower starting dose in newborns at risk for cardiac failure. Increase the dose every 4 to 6 weeks as needed based on clinical and laboratory response.

Children at risk for hyperactivity: To minimize the risk of hyperactivity in children, start at one-fourth the recommended full replacement dose, and increase on a weekly basis by one-fourth the full recommended replacement dose until the full recommended replacement dose is reached.

Pregnancy

Pre-existing Hypothyroidism:THYQUIDITY dose requirements may increase during pregnancy. Measure serum TSH and free-T4 as soon as pregnancy is confirmed and, at a minimum, during each trimester of pregnancy. In patients with primary hypothyroidism, maintain serum TSH in the trimester-specific reference range. For patients with serum TSH above the normal trimester- specific range, increase the dose of THYQUIDITY by 12.5 to 25 mcg/day and measure TSH every 4 weeks until a stable THYQUIDITY dose is reached and serum TSH is within the normal trimester-specific range. Reduce THYQUIDITY dosage to pre-pregnancy levels immediately after delivery and measure serum TSH levels 4 to 8 weeks postpartum to ensure THYQUIDITY dose is appropriate.

New Onset Hypothyroidism: Normalize thyroid function as rapidly as possible. Evaluate serum TSH every 4 weeks and adjust THYQUIDITY dosage until a serum TSH is within the normal trimester specific range [see Use in Specific Populations (8.1)].

TSH Suppression in Well-differentiated Thyroid Cancer

Generally, TSH is suppressed to below 0.1 mIU per liter, and this usually requires a THYQUIDITY dose of greater than 2 mcg per kg per day. However, in patients with high-risk tumors, the target level for TSH suppression may be lower.

2.4 Monitoring TSH and/or Thyroxine (T4) Levels

Assess the adequacy of therapy by periodic assessment of laboratory tests and clinical evaluation. Persistent clinical and laboratory evidence of hypothyroidism, despite an apparent adequate replacement dose of THYQUIDITY, may be evidence of inadequate absorption, poor compliance, drug interactions, or a combination of these factors.

Adults

In adult patients with primary hypothyroidism, monitor serum TSH levels after an interval of 6 to 8 weeks after any change in dose. In patients on a stable and appropriate replacement dose, evaluate clinical and biochemical response every 6 to 12 months and whenever there is a change in the patient's clinical status.

Pediatrics

In patients with congenital hypothyroidism, assess the adequacy of replacement therapy by measuring both serum TSH and total or free-T4. Monitor TSH and total or free-T4 in children as follows: 2 and 4 weeks after the initiation of treatment, 2 weeks after any change in dosage, and then every 3 to 12 months thereafter following dose stabilization until growth is completed. Poor compliance or abnormal values may necessitate more frequent monitoring. Perform routine clinical examination, including assessment of development, mental and physical growth, and bone maturation, at regular intervals.

Although the general aim of therapy is to normalize the serum TSH level, TSH may not normalize in some patients due to in uterohypothyroidism causing a resetting of pituitary-thyroid feedback. Failure of the serum T4 to increase into the upper half of the normal range within 2 weeks of initiation of THYQUIDITY therapy and/or of the serum TSH to decrease below 20 mIU per liter within 4 weeks may indicate the child is not receiving adequate therapy. Assess compliance, dose of medication administered, and method of administration prior to increasing the dose of THYQUIDITY [see Warnings and Precautions (5.4)and Use in Specific Populations (8.4)].

Secondary and Tertiary Hypothyroidism

Monitor serum free-T4 levels and maintain in the upper half of the normal range in these patients.

3 DOSAGE FORMS AND STRENGTHS

Oral Solution: 100 mcg per 5 mL (20 mcg per mL) clear, colorless to nearly colorless solution in 100 mL bottles

THYQUIDITY is to be used with a calibrated oral syringe provided by the pharmacy.

4 CONTRAINDICATIONS

THYQUIDITY is contraindicated in patients with:

- Uncorrected adrenal insufficiency [see Warnings and Precautions (5.3)].

5 WARNINGS AND PRECAUTIONS

5.1 Cardiac Adverse Reactions in the Elderly and in Patients with Underlying Cardiovascular Disease

Over-treatment with levothyroxine may cause an increase in heart rate, cardiac wall thickness, and cardiac contractility and may precipitate angina or arrhythmias, particularly in patients with cardiovascular disease and in elderly patients. Initiate THYQUIDITY therapy in this population at lower doses than those recommended in younger individuals or in patients without cardiac disease [see Dosage and Administration (2.3), Use in Specific Populations (8.5)].

Monitor for cardiac arrhythmias during surgical procedures in patients with coronary artery disease receiving suppressive THYQUIDITY therapy. Monitor patients receiving concomitant THYQUIDITY and sympathomimetic agents for signs and symptoms of coronary insufficiency.

If cardiac symptoms develop or worsen, reduce the THYQUIDITY dose or withhold for one week and restart at a lower dose.

5.2 Myxedema Coma

Myxedema coma is a life-threatening emergency characterized by poor circulation and hypometabolism, and may result in unpredictable absorption of levothyroxine sodium from the gastrointestinal tract. Use of oral thyroid hormone drug products is not recommended to treat myxedema coma. Administer thyroid hormone products formulated for intravenous administration to treat myxedema coma.

5.3 Acute Adrenal Crisis in Patients with Concomitant Adrenal Insufficiency

Thyroid hormone increases metabolic clearance of glucocorticoids. Initiation of thyroid hormone therapy prior to initiating glucocorticoid therapy may precipitate an acute adrenal crisis in patients with adrenal insufficiency. Treat patients with adrenal insufficiency with replacement glucocorticoids prior to initiating treatment with THYQUIDITY [see Contraindications (4)].

5.4 Prevention of Hyperthyroidism or Incomplete Treatment of Hypothyroidism

THYQUIDITY has a narrow therapeutic index. Over- or undertreatment with THYQUIDITY may have negative effects on growth and development, cardiovascular function, bone metabolism, reproductive function, cognitive function, emotional state, gastrointestinal function, and glucose and lipid metabolism [see Use in Specific Populations - Pediatric Use (8.4)] . Titrate the dose of THYQUIDITY carefully and monitor response to titration to avoid these effects [see Dosage and Administration (2.4)]. Monitor for the presence of drug or food interactions when using THYQUIDITY and adjust the dose as necessary [see Drug Interactions (7.9) and Clinical Pharmacology (12.3)].

5.5 Worsening of Diabetic Control

Addition of levothyroxine therapy in patients with diabetes mellitus may worsen glycemic control and result in increased antidiabetic agent or insulin requirements. Carefully monitor glycemic control after starting, changing, or discontinuing THYQUIDITY [see Drug Interactions (7.2)] .

5.6 Decreased Bone Mineral Density Associated with Thyroid Hormone Over-Replacement

Increased bone resorption and decreased bone mineral density may occur as a result of levothyroxine over-replacement, particularly in post-menopausal women. The increased bone resorption may be associated with increased serum levels and urinary excretion of calcium and phosphorous, elevations in bone alkaline phosphatase, and suppressed serum parathyroid hormone levels. Administer the minimum dose of THYQUIDITY that achieves the desired clinical and biochemical response to mitigate this risk.

6 ADVERSE REACTIONS

Adverse reactions associated with THYQUIDITY therapy are primarily those of hyperthyroidism due to therapeutic overdosage [see Warnings and Precautions (5), Overdosage (10)]. They include the following:

- General:fatigue, increased appetite, weight loss, heat intolerance, fever, excessive sweating
- Central nervous system:headache, hyperactivity, nervousness, anxiety, irritability, emotional lability, insomnia
- Musculoskeletal:tremors, muscle weakness, muscle spasm
- Cardiovascular:palpitations, tachycardia, arrhythmias, increased pulse and blood pressure, heart failure, angina, myocardial infarction, cardiac arrest
- Respiratory:dyspnea
- Gastrointestinal:diarrhea, vomiting, abdominal cramps, elevations in liver function tests
- Dermatologic:hair loss, flushing, rash
- Endocrine:decreased bone mineral density
- Reproductive:menstrual irregularities, impaired fertility

Seizures have been reported rarely with the institution of levothyroxine therapy.

Adverse Reactions in Children

Pseudotumor cerebri and slipped capital femoral epiphysis have been reported in children receiving levothyroxine therapy. Overtreatment may result in craniosynostosis in infants and premature closure of the epiphyses in children with resultant compromised adult height.

Hypersensitivity Reactions

Hypersensitivity reactions to inactive ingredients have occurred in patients treated with thyroid hormone products. These include urticaria, pruritus, skin rash, flushing, angioedema, various gastrointestinal symptoms (abdominal pain, nausea, vomiting and diarrhea), fever, arthralgia, serum sickness, and wheezing. Hypersensitivity to levothyroxine itself is not known to occur.

7 DRUG INTERACTIONS

7.1 Drugs Known to Affect Thyroid Hormone Pharmacokinetics

Many drugs can exert effects on thyroid hormone pharmacokinetics (e.g., absorption, synthesis, secretion, metabolism, protein binding, and target tissue response) and may alter the therapeutic response to THYQUIDITY (see Tables 2-5 below).

Table 2. Drugs That May Decrease T4 Absorption (Hypothyroidism)

Potential impact: Concurrent use may reduce the efficacy of THYQUIDITY by binding and delaying or preventing absorption, potentially resulting in hypothyroidism.
Drug or Drug Class | Effect
Calcium Carbonate Ferrous Sulfate | Calcium carbonate may form an insoluble chelate with levothyroxine, and ferrous sulfate likely forms a ferric- thyroxine complex. Administer THYQUIDITY at least 4 hours apart from these agents.
Orlistat | Monitor patients treated concomitantly with orlistat and THYQUIDITY for changes in thyroid function.
Bile Acid Sequestrants; -Colesevelam; -Cholestyramine; -Colestipol; Ion Exchange Resins; -Kayexalate; -Sevelamer | Bile acid sequestrants and ion exchange resins are known to decrease levothyroxine absorption. Administer THYQUIDITY at least 4 hours prior to these drugs or monitor TSH levels.
Other drugs:; Proton Pump Inhibitors; Sucralfate; Antacids; - Aluminum & Magnesium; Hydroxides; - Simethicone | Gastric acidity is an essential requirement for adequate absorption of levothyroxine. Sucralfate, antacids and proton pump inhibitors may cause hypochlorhydria, affect intragastric pH, and reduce levothyroxine absorption. Monitor patients appropriately.

Table 3. Drugs That May Alter T4 and Triiodothyronine (T3) Serum Transport Without Affecting Free Thyroxine (FT4) Concentration (Euthyroidism)

Drug or Drug Class | Effect
Clofibrate; Estrogen-containing oral contraceptives; Estrogens (oral); Heroin / Methadone; 5-Fluorouracil; Mitotane; Tamoxifen | These drugs may increase serum thyroxine-binding globulin (TBG) concentration.
Androgens / Anabolic Steroids Asparaginase; Glucocorticoids; Slow-Release Nicotinic Acid | These drugs may decrease serum TBG concentration.
Potential impact (below): Administration of these agents with THYQUIDITY results in an initial transient increase in FT4. Continued administration results in a decrease in serum T4 and normal FT4 and TSH concentrations.
Salicylates (> 2 g/day) | Salicylates inhibit binding of T4 and T3 to TBG and transthyretin. An initial increase in serum FT4 is followed by return of FT4 to normal levels with sustained therapeutic serum salicylate concentrations, although total T4 levels may decrease by as much as 30%.
Other drugs: Carbamazepine Furosemide (> 80 mg IV); Heparin; Hydantoins; Non-Steroidal Anti-inflammatory Drugs; -Fenamates | These drugs may cause protein-binding site displacement. Furosemide has been shown to inhibit the protein binding of T4 to TBG and albumin, causing an increase free T4 fraction in serum. Furosemide competes for T4-binding sites on TBG, prealbumin, and albumin, so that a single high dose can acutely lower the total T4 level. Phenytoin and carbamazepine reduce serum protein binding of levothyroxine, and total and free T4 may be reduced by 20% to 40%, but most patients have normal serum TSH levels and are clinically euthyroid.; Closely monitor thyroid hormone parameters.

Table 4. Drugs That May Alter Hepatic Metabolism of T4 (Hypothyroidism)

Potential impact: Stimulation of hepatic microsomal drug-metabolizing enzyme activity may cause increased hepatic degradation of levothyroxine, resulting in increased THYQUIDITY requirements.
Drug or Drug Class | Effect
Phenobarbital; Rifampin | Phenobarbital has been shown to reduce the response to thyroxine. Phenobarbital increases L-thyroxine metabolism by inducing uridine 5'-diphospho-glucuronosyltransferase (UGT) and leads to a lower T4 serum levels. Changes in thyroid status may occur if barbiturates are added or withdrawn from patients being treated for hypothyroidism. Rifampin has been shown to accelerate the metabolism of levothyroxine.

Table 5. Drugs That May Decrease Conversion of T4 to T3

Potential impact: Administration of these enzyme inhibitors decreases the peripheral conversion of T4 to T3, leading to decreased T3 levels. However, serum T4 levels are usually normal but may occasionally be slightly increased.
Drug or Drug Class | Effect
Beta-adrenergic antagonists (e.g., Propranolol > 160 mg/day) | In patients treated with large doses of propranolol (> 160 mg/day), T3 and T4 levels change, TSH levels remain normal, and patients are clinically euthyroid. Actions of particular beta-adrenergic antagonists may be impaired when the hypothyroid patient is converted to the euthyroid state.
Glucocorticoids; (e.g., Dexamethasone >4 mg/day) | Short-term administration of large doses of glucocorticoids may decrease serum T3 concentrations by 30% with minimal change in serum T4 levels. However, long-term glucocorticoid therapy may result in slightly decreased T3 and T4 levels due to decreased TBG production (See above).
Other drugs: Amiodarone | Amiodarone inhibits peripheral conversion of levothyroxine (T4) to triiodothyronine (T3) and may cause isolated biochemical changes (increase in serum free-T4, and decrease or normal free-T3) in clinically euthyroid patients.

7.2 Antidiabetic Therapy

Addition of THYQUIDITY therapy in patients with diabetes mellitus may worsen glycemic control and result in increased antidiabetic agent or insulin requirements. Carefully monitor glycemic control, especially when thyroid therapy is started, changed, or discontinued [see Warnings and Precautions (5.5)].

7.3 Oral Anticoagulants

THYQUIDITY increases the response to oral anticoagulant therapy. Therefore, a decrease in the dose of anticoagulant may be warranted with correction of the hypothyroid state or when the THYQUIDITY dose is increased. Closely monitor coagulation tests to permit appropriate and timely dosage adjustments.

7.4 Digitalis Glycosides

THYQUIDITY may reduce the therapeutic effects of digitalis glycosides. Serum digitalis glycoside levels may decrease when a hypothyroid patient becomes euthyroid, necessitating an increase in the dose of digitalis glycosides.

7.5 Antidepressant Therapy

Concurrent use of tricyclic (e.g., amitriptyline) or tetracyclic (e.g., maprotiline) antidepressants and THYQUIDITY may increase the therapeutic and toxic effects of both drugs, possibly due to increased receptor sensitivity to catecholamines. Toxic effects may include increased risk of cardiac arrhythmias and central nervous system stimulation. THYQUIDITY may accelerate the onset of action of tricyclics. Administration of sertraline in patients stabilized on THYQUIDITY may result in increased THYQUIDITY requirements.

7.6 Ketamine

Concurrent use of ketamine and THYQUIDITY may produce marked hypertension and tachycardia. Closely monitor blood pressure and heart rate in these patients.

7.7 Sympathomimetics

Concurrent use of sympathomimetics and THYQUIDITY may increase the effects of sympathomimetics or thyroid hormone. Thyroid hormones may increase the risk of coronary insufficiency when sympathomimetic agents are administered to patients with coronary artery disease.

7.8 Tyrosine-Kinase Inhibitors

Concurrent use of tyrosine-kinase inhibitors such as imatinib may cause hypothyroidism. Closely monitor TSH levels in such patients.

7.9 Drug-Food Interactions

Consumption of certain foods may affect THYQUIDITY absorption thereby necessitating adjustments in dosing [see Dosage and Administration (2.1)]. Soybean products, such as infant formula and soybean flour, cottonseed meal, walnuts, and dietary fiber may bind and decrease the absorption of THYQUIDITY from the gastrointestinal tract. Grapefruit juice may delay the absorption of levothyroxine and reduce its bioavailability.

7.10 Drug-Laboratory Test Interactions

Consider changes in TBG concentration when interpreting T4 and T3 values. Measure and evaluate unbound (free) hormone and/or determine the free-T4 index (FT4I) in this circumstance. Pregnancy, infectious hepatitis, estrogens, estrogen-containing oral contraceptives, and acute intermittent porphyria increase TBG concentration. Nephrosis, severe hypoproteinemia, severe liver disease, acromegaly, androgens, and corticosteroids decrease TBG concentration. Familial hyper- or hypo-thyroxine binding globulinemias have been described, with the incidence of TBG deficiency approximating 1 in 9000.

8 USE IN SPECIFIC POPULATIONS

8.1 Pregnancy

Risk Summary

Prolonged experience with levothyroxine use in pregnant women, including data from post-marketing studies, to maintain a euthyroid state have not reported increased rates of major birth defects, miscarriages, or adverse maternal or fetal outcomes .There are risks to the mother and fetus associated with untreated hypothyroidism in pregnancy. Since TSH levels may increase during pregnancy, TSH should be monitored and THYQUIDITY dosage adjusted during pregnancy (see Clinical Considerations) . There are no animal studies conducted with levothyroxine during pregnancy. THYQUIDITY should not be discontinued during pregnancy and hypothyroidism diagnosed during pregnancy should be promptly treated.

The estimated background risk of major birth defects and miscarriage for the indicated population is unknown. All pregnancies have a background risk of birth defect, loss or other adverse outcomes. In the U.S. general population, the estimated background risk of major birth defects and miscarriage in clinically recognized pregnancies is 2 to 4% and 15 to 20%, respectively.

Clinical Considerations

Disease-Associated Maternal and/or Embryo/Fetal Risk

Maternal hypothyroidism during pregnancy is associated with a higher rate of complications, including spontaneous abortion, gestational hypertension, pre-eclampsia, stillbirth, and premature delivery. Untreated maternal hypothyroidism may have an adverse effect on fetal neurocognitive development.

Dose Adjustments During Pregnancy and the Postpartum Period

Pregnancy may increase THYQUIDITY requirements. Serum TSH levels should be monitored and the THYQUIDITY dosage adjusted during pregnancy to maintain TSH within normal trimester specific ranges. Since postpartum TSH levels are similar to preconception values, the THYQUIDITY dosage should return to the pre-pregnancy dose immediately after delivery [see Dosage and Administration (2.3)].

8.2 Lactation

Risk Summary

Limited published studies report that levothyroxine is present in human milk. No adverse effects on the breastfed infant have been reported and there is no information on the effects of levothyroxine on milk production. Adequate levothyroxine treatment during lactation may normalize milk production in hypothyroid lactating mothers with low milk supply. The developmental and health benefits of breastfeeding should be considered along with the mother's clinical need for THYQUIDITY and any potential adverse effects on the breastfed infant from THYQUIDITY or from the underlying maternal condition.

8.4 Pediatric Use

Safety and effectiveness of THYQUIDITY has been established for the treatment of congenital hypothyroidism and acquired hypothyroidism in pediatric patients down to birth [see Adverse Reactions (6)].

Glycerol has the potential to cause gastrointestinal irritation resulting in vomiting and/or osmotic diarrhea. Patients in the first 3 months of life may be particularly susceptible to serious fluid and electrolyte complications from glycerol-induced gastrointestinal irritation. Closely monitor patients from birth to 3 months of age receiving THYQUIDITY for signs and symptoms of gastrointestinal irritation.

Congenital Hypothyroidism [see Dosage and Administration (2.3,2.4)]

Rapid restoration of normal serum T4 concentrations is essential for preventing the adverse effects of congenital hypothyroidism on intellectual development as well as on overall physical growth and maturation. Therefore, initiate THYQUIDITY therapy immediately upon diagnosis. Levothyroxine is generally continued for life in these patients.

Closely monitor patients during the first 2 weeks of THYQUIDITY therapy for cardiac overload, arrhythmias, and aspiration from avid suckling.

Closely monitor patients to avoid undertreatment or overtreatment. Undertreatment may have deleterious effects on intellectual development and linear growth. Overtreatment is associated with craniosynostosis in infants, may adversely affect the tempo of brain maturation, and may accelerate the bone age and result in premature epiphyseal closure and compromised adult stature.

Acquired Hypothyroidism in Pediatric Patients

Closely monitor patients to avoid undertreatment and overtreatment. Undertreatment may result in poor school performance due to impaired concentration and slowed mentation and in reduced adult height. Overtreatment may accelerate the bone age and result in premature epiphyseal closure and compromised adult stature.

Treated children may manifest a period of catch-up growth, which may be adequate in some cases to normalize adult height. In children with severe or prolonged hypothyroidism, catch-up growth may not be adequate to normalize adult height.

8.5 Geriatric Use

Because of the increased prevalence of cardiovascular disease among the elderly, initiate THYQUIDITY at less than the full replacement dose [see Warnings and Precautions (5.1)and Dosage and Administration (2.3)]. Atrial arrhythmias can occur in elderly patients. Atrial fibrillation is the most common of the arrhythmias observed with levothyroxine overtreatment in the elderly.

10 OVERDOSAGE

The signs and symptoms of overdosage are those of hyperthyroidism [see Warnings and Precautions (5)and Adverse Reactions (6)]. In addition, confusion and disorientation may occur. Cerebral embolism, shock, coma, and death have been reported. Seizures occurred in a 3-year old child ingesting 3.6 mg of levothyroxine. Symptoms may not necessarily be evident or may not appear until several days after ingestion of levothyroxine sodium.

Reduce the THYQUIDITY dose or discontinue temporarily if signs or symptoms of overdosage occur. Initiate appropriate supportive treatment as dictated by the patient's medical status. For current information on the management of poisoning or overdosage, contact the National Poison Control Center at 1-800-222-1222 or www.poison.org.

11 DESCRIPTION

THYQUIDITY (levothyroxine sodium) oral solution contains synthetic L-3,3',5,5'-tetraiodothyronine sodium salt [levothyroxine (T4) sodium]. Synthetic T4 is chemically identical to that produced in the human thyroid gland, and is very slightly soluble in water. Levothyroxine (T4) sodium hydrate has an empirical formula of C15H10I4NNaO4• xH2O, molecular weight of 798.85 (anhydrous), and structural formula as shown:

THYQUIDITY oral solution is supplied in the following strength: 100 mcg per 5 mL (20 mcg per mL). THYQUIDITY oral solution contains the inactive ingredients citric acid monohydrate, glycerin, methylparaben sodium, sodium hydroxide and purified water.

12 CLINICAL PHARMACOLOGY

12.1 Mechanism of Action

Thyroid hormones exert their physiologic actions through control of DNA transcription and protein synthesis. Triiodothyronine (T3) and L-thyroxine (T4) diffuse into the cell nucleus and bind to thyroid receptor proteins attached to DNA. This hormone nuclear receptor complex activates gene transcription and synthesis of messenger RNA and cytoplasmic proteins.

The physiological actions of thyroid hormones are produced predominantly by T3, the majority of which (approximately 80%) is derived from T4 by deiodination in peripheral tissues.

12.2 Pharmacodynamics

Oral levothyroxine sodium is a synthetic T4 hormone that exerts the same physiologic effect as endogenous T4, thereby maintaining normal T4 levels when a deficiency is present.

12.3 Pharmacokinetics

Absorption

Absorption of orally administered T4 from the gastrointestinal tract ranges from 40% to 80%. The majority of the THYQUIDITY dose is absorbed from the jejunum and upper ileum. T4 absorption is increased by fasting, and decreased in malabsorption syndromes and by certain foods such as soybeans. Dietary fiber decreases bioavailability of T4. Absorption may also decrease with age. In addition, many drugs and foods affect T4 absorption [see Drug Interactions (7)].

Distribution

Circulating thyroid hormones are greater than 99% bound to plasma proteins, including thyroxine-binding globulin (TBG), thyroxine-binding prealbumin (TBPA), and thyroxine-binding albumin (TBA), whose capacities and affinities vary for each hormone. The higher affinity of both TBG and TBPA for T4 partially explains the higher serum levels, slower metabolic clearance, and longer half-life of T4 compared to T3. Protein-bound thyroid hormones exist in reverse equilibrium with small amounts of free hormone. Only unbound hormone is metabolically active. Many drugs and physiologic conditions affect the binding of thyroid hormones to serum proteins [see Drug Interactions (7)]. Thyroid hormones do not readily cross the placental barrier [see Use in Specific Populations (8.1)].

Elimination

Metabolism

T4 is slowly eliminated (see Table 6). The major pathway of thyroid hormone metabolism is through sequential deiodination. Approximately 80% of circulating T3 is derived from peripheral T4 by monodeiodination. The liver is the major site of degradation for both T4 and T3, with T4 deiodination also occurring at a number of additional sites, including the kidney and other tissues. Approximately 80% of the daily dose of T4 is deiodinated to yield equal amounts of T3 and reverse T3 (rT3). T3 and rT3 are further deiodinated to diiodothyronine. Thyroid hormones are also metabolized via conjugation with glucuronides and sulfates and excreted directly into the bile and gut where they undergo enterohepatic recirculation.

Excretion

Thyroid hormones are primarily eliminated by the kidneys. A portion of the conjugated hormone reaches the colon unchanged and is eliminated in the feces. Approximately 20% of T4 is eliminated in the stool. Urinary excretion of T4 decreases with age.

Table 6. Pharmacokinetic Parameters of Thyroid Hormones in Euthyroid Patients

Hormone | Ratio in Thyroglobulin | Biologic Potency | Half-Life (days) | Protein Binding (%)a
Levothyroxine (T4) | 10 - 20 | 1 | 6-7b | 99.96
Liothyronine (T3) | 1 | 4 | ≤ 2 | 99.5
aIncludes TBG, TBPA, and TBA
b3 to 4 days in hyperthyroidism, 9 to 10 days in hypothyroidism

13 NONCLINICAL TOXICOLOGY

13.1 Carcinogenesis, Mutagenesis, Impairment of Fertility

Standard animal studies have not been performed to evaluate the carcinogenic potential, mutagenic potential or effects on fertility of levothyroxine.

16 HOW SUPPLIED/STORAGE AND HANDLING

THYQUIDITY (levothyroxine sodium) oral solution, 100 mcg per 5 mL (20 mcg per mL) is a clear, colorless to nearly colorless solution supplied in a 100 mL amber glass bottle with a child-resistant closure as follows:

NDC 82685-360-01: 1 x 100 mL bottle
NDC 82685-360-02: 2 x 100 mL bottles (NDC 82685-360-01)

The pharmacy will provide a calibrated oral syringe to accurately measure the prescribed dose.

Storage Conditions

Store at 20°C to 25°C (68°F to 77°F) [see USP Controlled Room Temperature]. Protect from light.

Store and dispense in original bottle. Use within 8 weeks of opening the bottle.

17 PATIENT COUNSELING INFORMATION

Inform the patient of the following information to aid in the safe and effective use of THYQUIDITY:

Dosing and Administration

- Instruct patients to take THYQUIDITY only as directed by their healthcare provider.
- Instruct patients to take THYQUIDITY once daily, preferably on an empty stomach, one-half to one hour before breakfast.
- Instruct patients to always use a calibrated oral syringe provided by the pharmacy when administering THYQUIDITY to ensure that the dose is measured and administered accurately.
- Inform patients that agents such as iron and calcium supplements and antacids can decrease the absorption of levothyroxine. Instruct patients not to take THYQUIDITY within 4 hours of these agents.
- Instruct patients to notify their healthcare provider if they are pregnant or breastfeeding or are thinking of becoming pregnant while taking THYQUIDITY.

Important Information

- Inform patients that it may take several weeks before they notice an improvement in symptoms.
- Inform patients that the levothyroxine in THYQUIDITY is intended to replace a hormone that is normally produced by the thyroid gland. Generally, replacement therapy is to be taken for life.
- Inform patients that THYQUIDITY should not be used as a primary or adjunctive therapy in a weight control program.
- Instruct patients to notify their healthcare provider if they are taking any other medications, including prescription and over-the-counter preparations.
- Instruct patients to notify their physician of any other medical conditions they may have, particularly heart disease, diabetes, clotting disorders, and adrenal or pituitary gland problems, as the dose of medications used to control these other conditions may need to be adjusted while they are taking THYQUIDITY. If they have diabetes, instruct patients to monitor their blood and/or urinary glucose levels as directed by their physician and immediately report any changes to their physician. If patients are taking anticoagulants, their clotting status should be checked frequently.
- Instruct patients to notify their physician or dentist that they are taking THYQUIDITY prior to any surgery.

Adverse Reactions

- Instruct patients to notify their healthcare provider if they experience any of the following symptoms: rapid or irregular heartbeat, chest pain, shortness of breath, leg cramps, headache, nervousness, irritability, sleeplessness, tremors, change in appetite, weight gain or loss, vomiting, diarrhea, excessive sweating, heat intolerance, fever, changes in menstrual periods, hives or skin rash, or any other unusual medical event.
- Inform patients that partial hair loss may occur rarely during the first few months of THYQUIDITY therapy, but this is usually temporary.

Distributed by:

Oliva Therapeutics, LLC
Ridgewood, NJ 07450

For more information go to www.thyquidity.com

Thyquidity is a registered trademark of Jerome Stevens Pharmaceuticals, Inc.

Rev. 04/25 THY-PI-01

PRINCIPAL DISPLAY PANEL - 100 mL Bottle Label

NDC 82685-360-01
Rx Only

Thyquidity®
(levothyroxine sodium)
Oral Solution

100 micrograms/5 mL
(20 micrograms/mL)

For Oral Administration Only

PHARMACIST:Advise patients
to always use a calibrated oral
syringe provided by the
pharmacy when using this
product. Store and dispense
in original bottle.

100 mL

Oliva Therapeutics, LLC